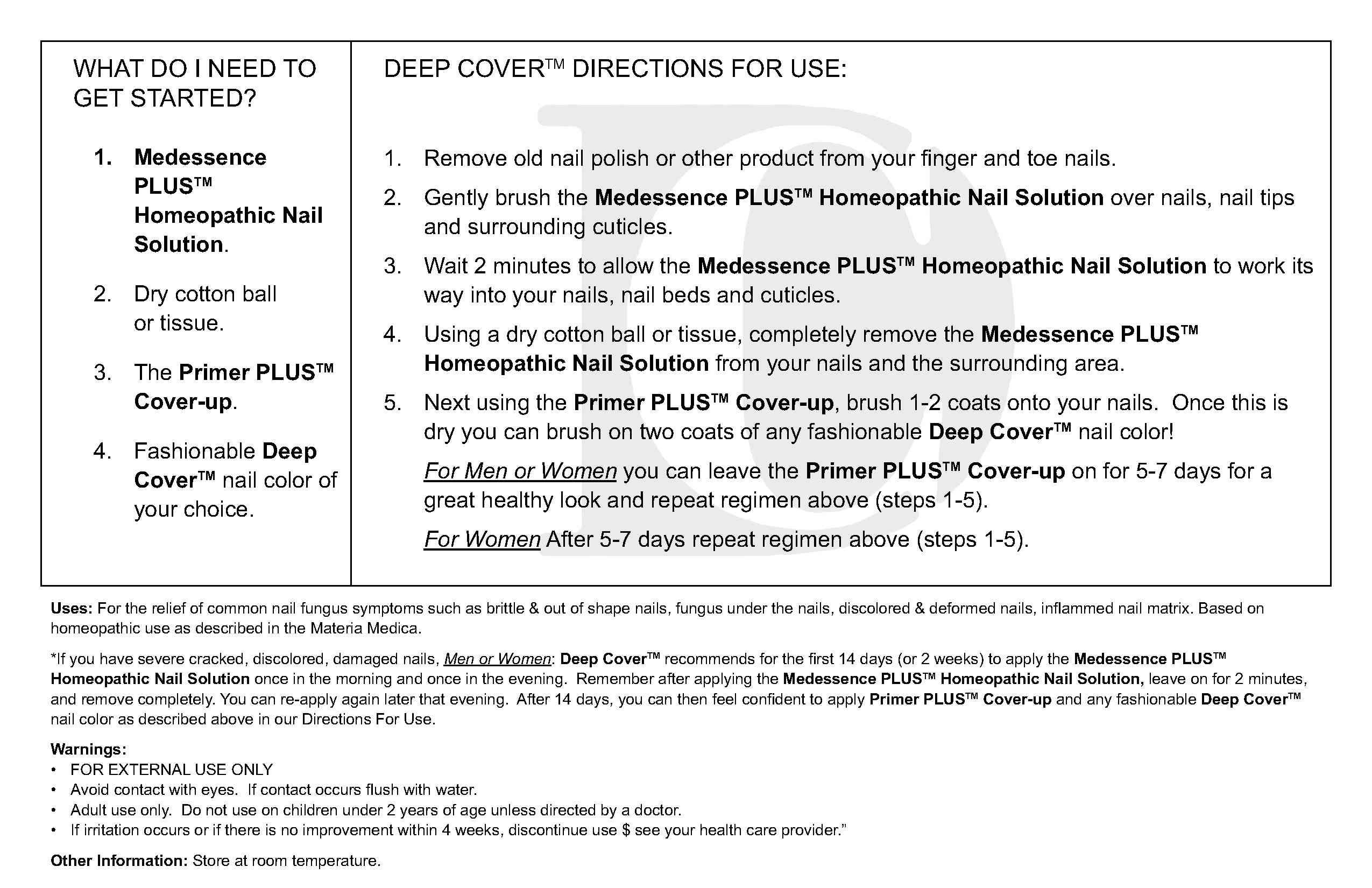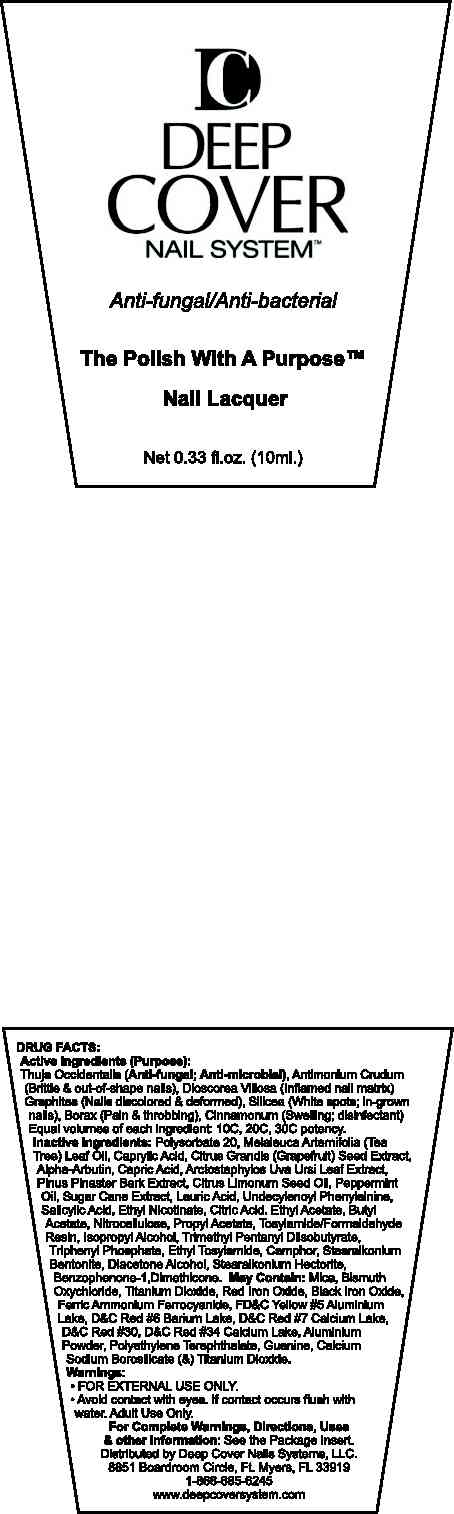 DRUG LABEL: Medessence Plus
NDC: 50125-001 | Form: SOLUTION
Manufacturer: Deep Cover Systems LLC
Category: homeopathic | Type: HUMAN OTC DRUG LABEL
Date: 20100126

ACTIVE INGREDIENTS: THUJA OCCIDENTALIS TWIG 10 [hp_X]/10 mL; ANTIMONY TRISULFIDE 10 [hp_X]/10 mL; DIOSCOREA VILLOSA EXTRACT 10 [hp_X]/10 mL; GRAPHITE 10 [hp_X]/10 mL; SILICON DIOXIDE 10 [hp_X]/10 mL; SODIUM BORATE 10 [hp_X]/10 mL; CINNAMON 10 [hp_X]/10 mL

Inactive Ingredients:

Polysorbate 20, Melaleuca Artenrifolia (Tea Trea) Leaf Oil, Caprylic Acid, Citrus Grandis (Grapefruit) Seed Extract, Alpha-Arbutin, Capric Acid, Arctostaphylos Uva Ursi Leaf Extract, Pinus Pinaster Bark Extract, Citrus Limonum Seed Oil, Peppermint Oil, Sugar Cane Extract, Lauric Acid, Undecylenoyl Phenylalnine, Salicylic Acid, Ethyl Nicotinate, Citric Acid

Purpose:

Anti-fungal, anti-microbial

Brittle and out of shape nails

Inflamed nail matrix

nails discolored and deformed

white spots; in grown nails

pain and throbbing

swelling; disinfectant

Equal Volumes of each ingredient: 10C, 20C, 30C potency

Distributed By Deep Cover Systems LLC

8851 Boardroom Circle Ft Myers FL 33919

1-866-685-6245

www.deepcoversystem.com

WARNINGS

For External Use Only

Avoid contact with eyes. If contact occurs flush with water.

Intended for adult use only. Do not use on children under 2 years of age unless directed by a doctor

If irritation occurs or if there is no improvement within 4 weeks, discontinue use and see your health care provider

INDICATIONS AND USAGE

For Directions, uses and other information:

See the package insert

DOSAGE AND ADMINISTRATION

Deep Cover Directions for Use:

1. Remove old nail polish or other product from your finger and toe nails.

2. Gently brush the Medessence PLUS Homeopathic Nail Solution over nails, nail tips and surrounding cuticles.

3. Wait 2 minutes to allow the Medessence PLUS Homeopathic Nail Solution to work its way into your nails, nail beds and cuticles.

4. Using a dry cotton ball or tissue, completely remove Medessence PLUS Homeopathic Nail Solution from your nails and the surrounding area.

5. Next using the Primer PLUS Cover up, brush 1-2 coats onto your nails. Once this is dry you can brush on two coats of any
fashionable Deep Cover nail color.

For Men or Women you can leave the Primer PLUS Cover up on for 5-7 days for a great healthy look and repeat regimen above (steps 1-5).

For Women After 5-7 days repeat regimen above (steps 1-5).

What do I need to get started?
1. Medessence PLUS Homeopathic Nail Solution
2. Dry cotton ball or tissue.
3. The Primer PLUS Cover-up.
4. Fashionable Deep Cover nail color of your choice.

PACKAGE LABEL

Enter section text here